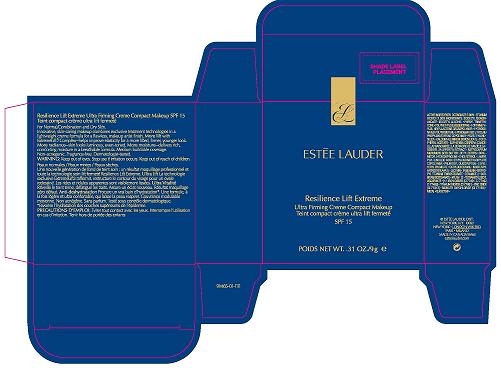 DRUG LABEL: RESILIENCE LIFT EXTREME CREME COMPACT MAKEUP 
NDC: 11559-720 | Form: CREAM
Manufacturer: ESTEE LAUDER INC
Category: otc | Type: HUMAN OTC DRUG LABEL
Date: 20100412

ACTIVE INGREDIENTS: OCTINOXATE 5.0 g/100 g; TITANIUM DIOXIDE 2.0 g/100 g

ACTIVE INGREDIENT: OCTINOXATE 5.0% [] TITANIUM DIOXIDE 2%

WARNINGS

WARNING: KEEP OUT OF EYES. STOP USE IF IRRITATION OCCURS. KEEP OUT OF REACH OF CHILDREN.

PACKAGE LABEL

PRINCIPAL DISPLAY PANEL

ESTEE LAUDER
RESILIENCE LIFT EXTREME
ULTRA FIRMING CREME COMPACT MAKEUP
SPF 15
NET WT. 0.31 OZ/ 9 GM
ESTEE LAUDER DIST
NEW YORK, NY 10022
9M65
ESTEE LAUDER.COM